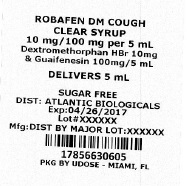 DRUG LABEL: Robafen DM Cough Sugar Free Clear
NDC: 17856-6306 | Form: SOLUTION
Manufacturer: Atlantic Biologicals Corps
Category: otc | Type: HUMAN OTC DRUG LABEL
Date: 20160722

ACTIVE INGREDIENTS: Guaifenesin 100 mg/5 mL; Dextromethorphan Hydrobromide 10 mg/5 mL
INACTIVE INGREDIENTS: Sodium Benzoate; Polyethylene Glycols; Anhydrous Citric Acid; Glycerin; Propylene glycol; Povidones; Menthol; Prunus Serotina Bark; Sucralose; Water

Robafen DM Cough Sugar Free Clear®

ACTIVE INGREDIENT

(in each TSP (5 mL)) Active ingredients | Purpose
Dextromethorphan HBr USP 10 mg | Cough suppressant
Guaifenesin USP 100 mg | Expectorant

Uses

- Temporarily relieves cough due to minor throat and bronchial irritation as may occour with a cold.
- Helps loosen phlegm (mucus) and thin bronchial secretions to drain bronchial tubes.

Warnings

DO NOT USE

if you are now taking a prescription monoamine oxidase inhibitor (MAOI) (certain drugs for depression, psychiatric or emotional conditions, or Parkinsons disease) or for 2 weeks after stopping the MAOI drug. If you do not know if your prescription drug contains MAOI, ask a doctor or pharmacist before taking this product. Do not use:

Ask a doctor before use if you have

- Cough that lasts or is chronic such as occurs with smoking, asthma, chronic bronchitis, or emphysema.
- Cough occurs with too much phlegm (mucus)

Stop use and ask a doctor if

Cough lasts more than 7 days, comes back or is accompanied by fever, rash, or persistent headache. These could be signs of a serious condition.

PREGNANCY OR BREAST FEEDING

ask a health professional before use. If pregnant or breast feeding:

KEEP OUT OF REACH OF CHILDREN

In case of overdose , get medical help or contact a Poison Control center right away. Keep out of reach of children.

Directions

Do not take more than 6 doses in any 24 hour period.

age | dose
Adults and children 12 years and over | 2 TSP (teaspoonful) every 4 hours
children under 12 years | do not use

Other information

- sodium- 2mg Each TSP (5ml) contains:
- Store at 20-25° C (68-77° F)
- Dosage cup provided

Inactive ingredients

artificial flavor, citric acid, glycerin, menthol, polyethylene glycol 1450, povidone, propylene glycol, purified water, sodium benzoate, sucralose.

Questions or Comments?

1-800-616-2471

Distributed by: 31778 Enterprise Drive Livonia, MI 48150 USA
MAJOR PHARMACEUTICALS®